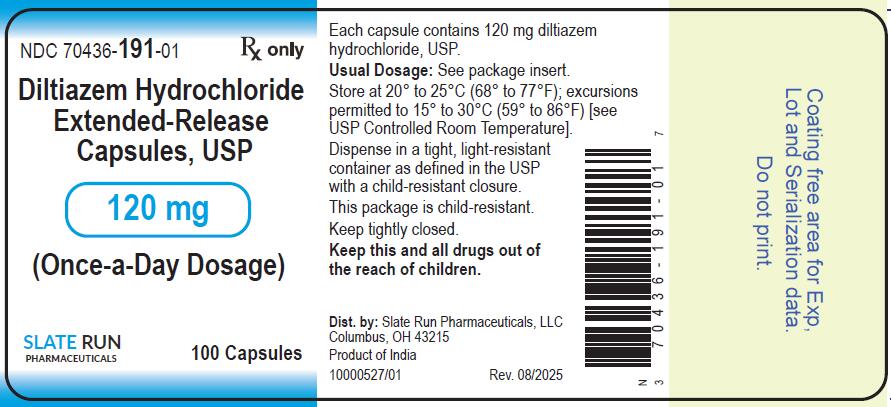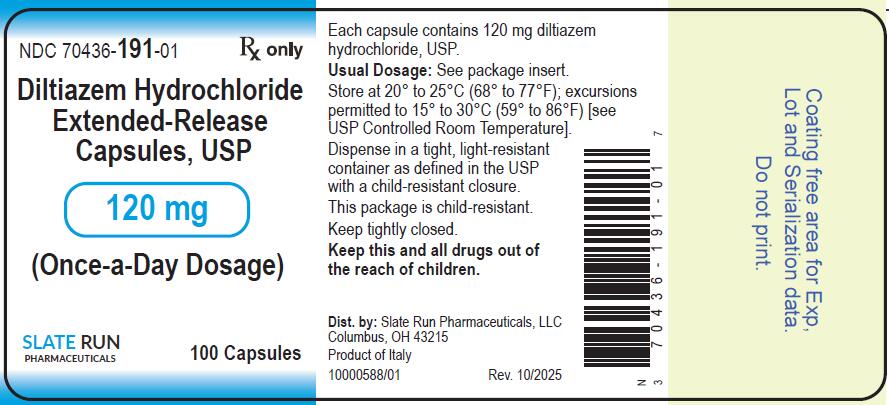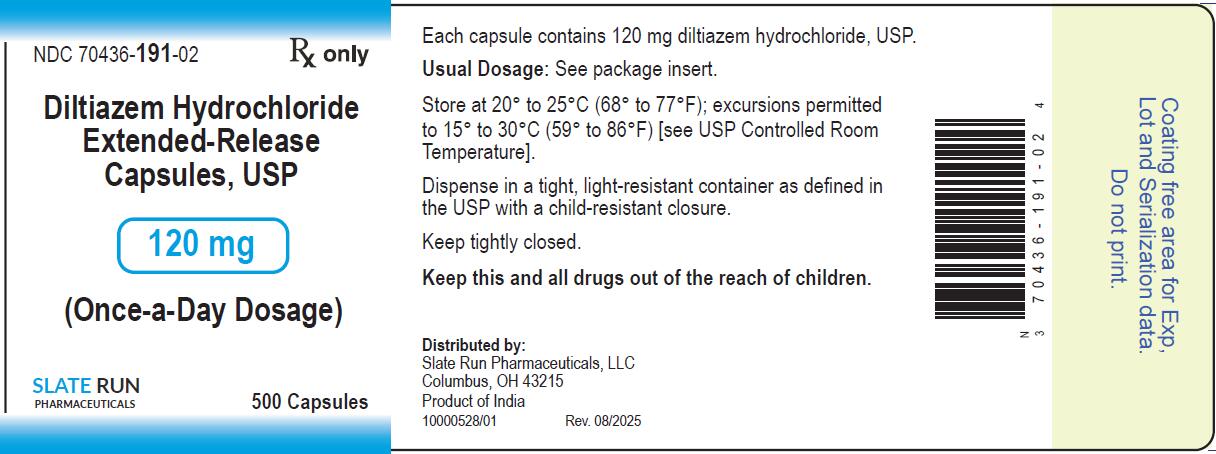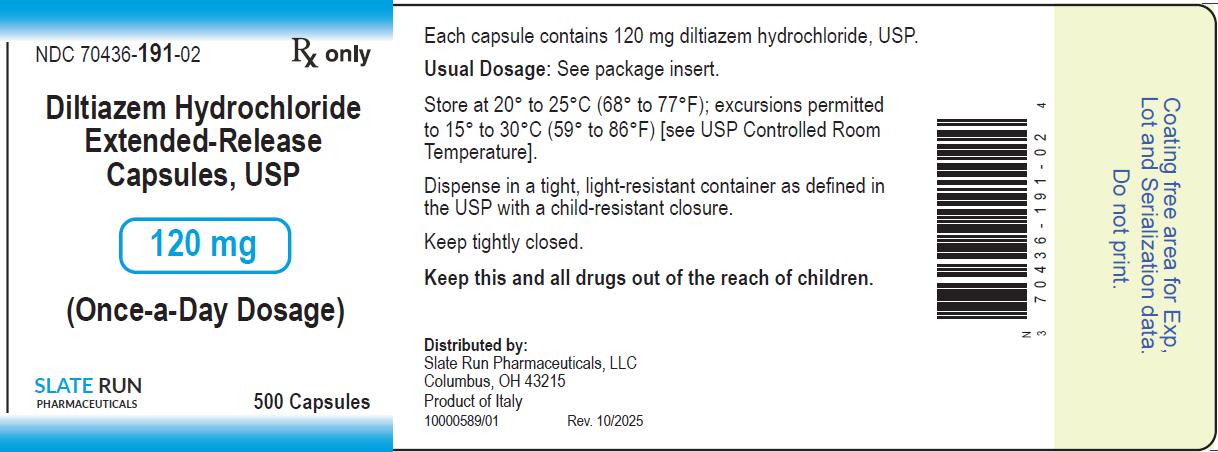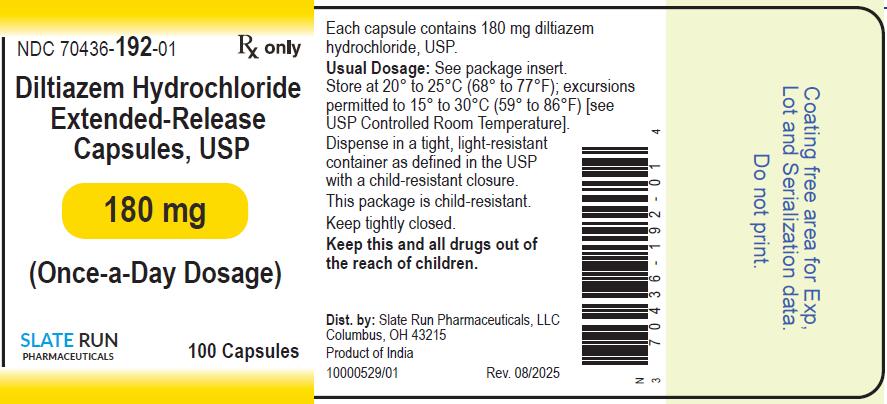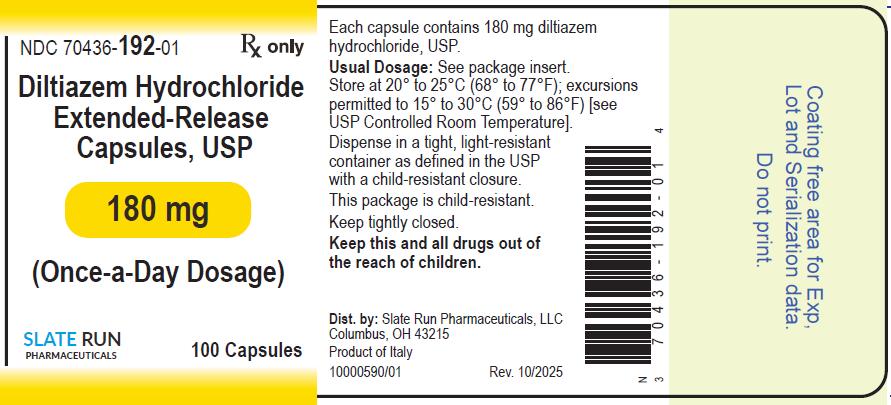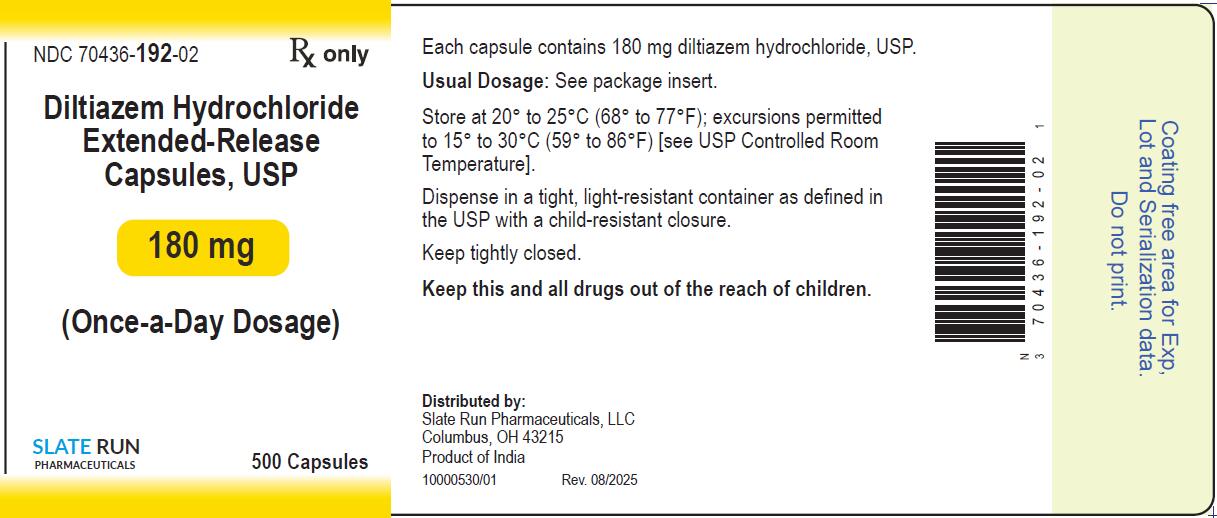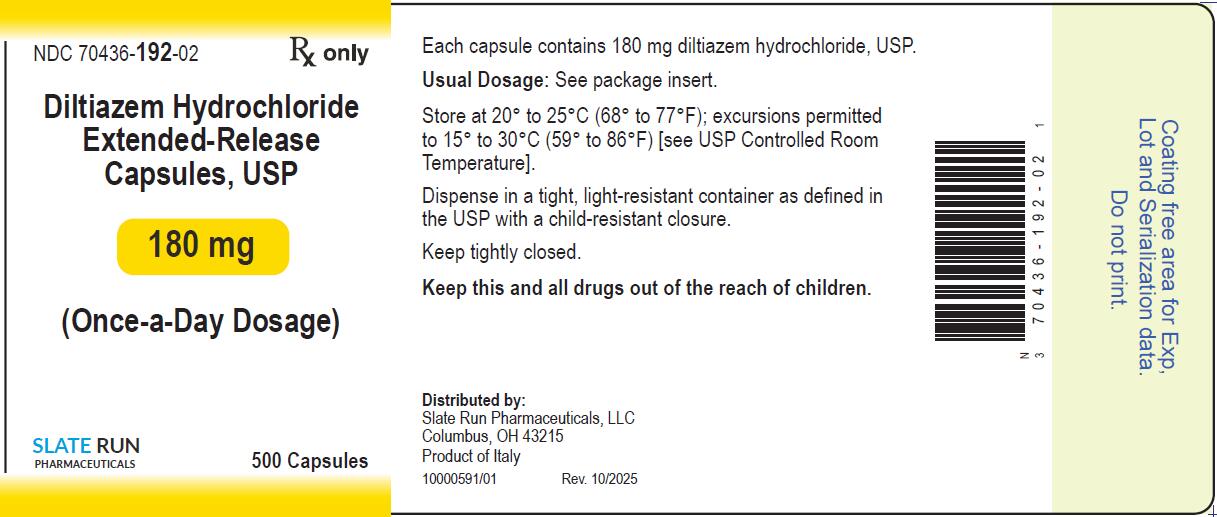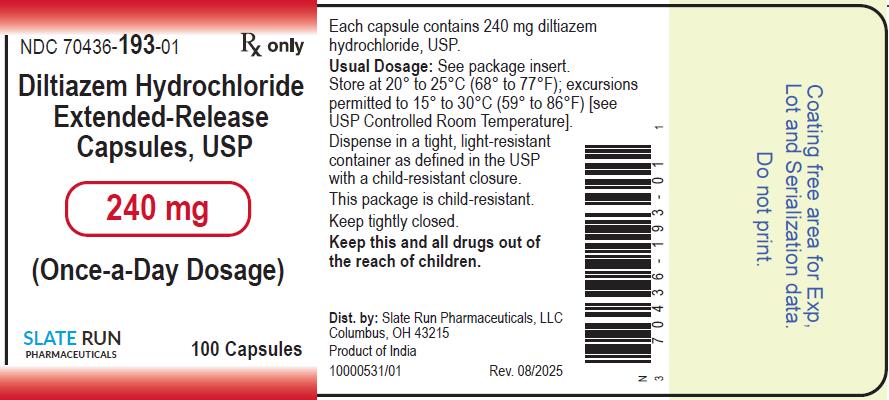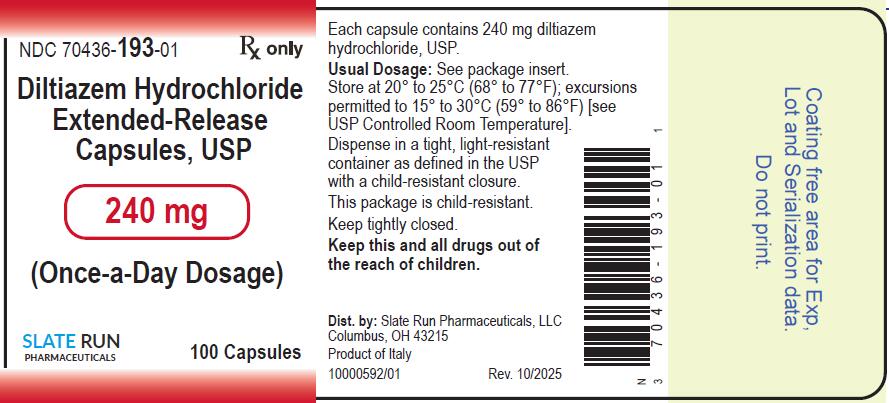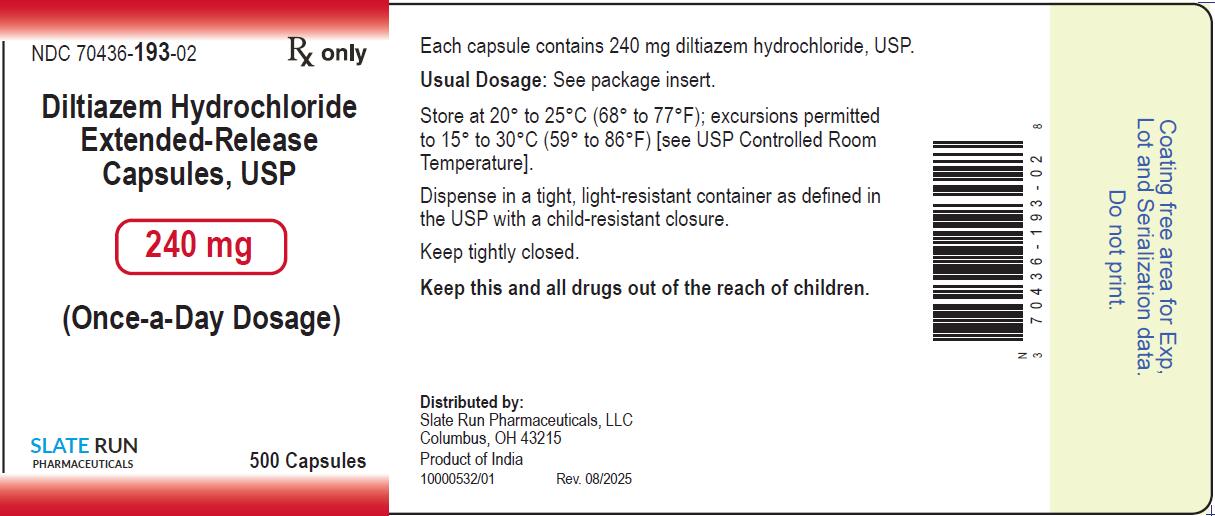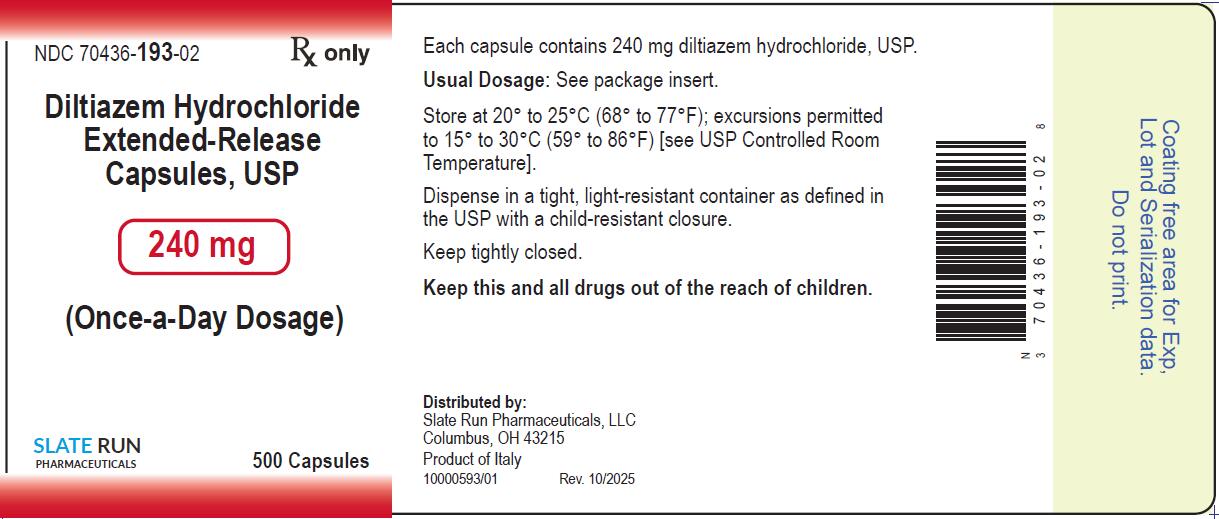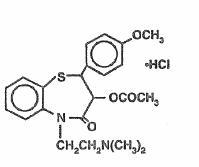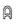 DRUG LABEL: Diltiazem Hydrochloride
NDC: 70436-191 | Form: CAPSULE, EXTENDED RELEASE
Manufacturer: Slate Run Pharmaceuticals, LLC
Category: prescription | Type: HUMAN PRESCRIPTION DRUG LABEL
Date: 20251201

ACTIVE INGREDIENTS: DILTIAZEM HYDROCHLORIDE 120 mg/1 1
INACTIVE INGREDIENTS: HYPROMELLOSES; SILICON DIOXIDE; MAGNESIUM STEARATE; GELATIN; TITANIUM DIOXIDE; ETHYLCELLULOSE AQUEOUS DISPERSION TYPE B; FERRIC OXIDE YELLOW

Diltiazem Hydrochloride Extended-Release Capsules, USP
Rx only

DESCRIPTION

Diltiazem Hydrochloride is a calcium ion influx inhibitor (slow channel blocker or calcium antagonist). Chemically, diltiazem hydrochloride is 1,5-Benzothiazepin-4(5 H)one, 3-(acetyloxy)-5-[2-(dimethylamino)ethyl]-2,3-dihydro-2-(4-methoxyphenyl)-, monohydrochloride, (+)-cis-. Its molecular formula is C22H26N2O4S•HCl and its molecular weight is 450.98. Its structural formula is as follows:

Diltiazem hydrochloride is a white to off-white crystalline powder with a bitter taste. It is soluble in water, methanol, and chloroform.

Diltiazem Hydrochloride Extended-Release Capsules, USP contain multiple units of diltiazem HCl extended-release 60 mg, resulting in 120 mg, 180 mg, or 240 mg dosage strengths allowing for the controlled release of diltiazem HCl over a 24-hour period.

Inactive Ingredients:Diltiazem Hydrochloride Extended-Release Capsules, USP also contain colloidal silicon dioxide, ethylcellulose, hypromellose, magnesium stearate, medium chain triglycerides and oleic acid.

The 120 mg, 180 mg and 240 mg capsule shells contain gelatin and titanium dioxide, ferric oxide yellow (120 mg and 180 mg), and ferric oxide red (180 mg and 240 mg).

The imprinting ink contains ferrosoferric oxide, potassium hydroxide and shellac.

For oral administration.

Diltiazem Hydrochloride Extended-Release Capsules, USP meet USP Dissolution Test 28.

CLINICAL PHARMACOLOGY

The therapeutic benefits of diltiazem hydrochloride are believed to be related to its ability to inhibit the influx of calcium ions during membrane depolarization of cardiac and vascular smooth muscles.

Mechanism of Action

Hypertension

Diltiazem hydrochloride produces its antihypertensive effect primarily by relaxation of vascular smooth muscle with a resultant decrease in peripheral vascular resistance. The magnitude of blood pressure reduction is related to the degree of hypertension; thus hypertensive individuals experience an antihypertensive effect, whereas there is only a modest fall in blood pressure in normotensives.

Angina

Diltiazem hydrochloride has been shown to produce increases in exercise tolerance, probably due to its ability to reduce myocardial oxygen demand. This is accomplished via reductions in heart rate and systemic blood pressure at submaximal and maximal work loads.

Diltiazem has been shown to be a potent dilator of coronary arteries, both epicardial and subendocardial. Spontaneous and ergonovine-induced coronary artery spasms are inhibited by diltiazem.

In animal models, diltiazem interferes with the slow inward (depolarizing) current in excitable tissue. It causes excitation-contraction uncoupling in various myocardial tissues without changes in the configuration of the action potential. Diltiazem produces relaxation of coronary vascular smooth muscle and dilation of both large and small coronary arteries at drug levels which cause little or no negative inotropic effect. The resultant increases in coronary blood flow (epicardial and subendocardial) occur in ischemic and nonischemic models and are accompanied by dose-dependent decreases in systemic blood pressure and decreases in peripheral resistance.

Hemodynamic and Electrophysiologic Effects

Like other calcium antagonists, diltiazem decreases sinoatrial and atrioventricular conduction in isolated tissues and has a negative inotropic effect in isolated preparations. In the intact animal, prolongation of the AH interval can be seen at higher doses.

In man, diltiazem prevents spontaneous and ergonovine-provoked coronary artery spasm. It causes a decrease in peripheral vascular resistance and a modest fall in blood pressure in normotensive individuals. In exercise tolerance studies in patients with ischemic heart disease, diltiazem reduces the double product (HR x SBP) for any given work load. Studies to date, primarily in patients with good ventricular function, have not revealed evidence of a negative inotropic effect. Cardiac output, ejection fraction and left ventricular end diastolic pressure have not been affected. Such data have no predictive value with respect to effects in patients with poor ventricular function. Increased heart failure has, however, been reported in occasional patients with pre-existing impairment of ventricular function. There are as yet few data on the interaction of diltiazem and beta-blockers in patients with poor ventricular function. Resting heart rate is usually slightly reduced by diltiazem.

Diltiazem hydrochloride extended-release capsules produce antihypertensive effects both in the supine and standing positions. Postural hypotension is infrequently noted upon suddenly assuming an upright position. Diltiazem decreases vascular resistance, increases cardiac output (by increasing stroke volume), and produces a slight decrease or no change in heart rate. No reflex tachycardia is associated with the chronic antihypertensive effects.

During dynamic exercise, increases in diastolic pressure are inhibited while maximum achievable systolic pressure is usually reduced. Heart rate at maximum exercise does not change or is slightly reduced.

Diltiazem antagonizes the renal and peripheral effects of angiotensin II. No increased activity of the renin-angiotensin-aldosterone axis has been observed. Chronic therapy with diltiazem produces no change or an increase in plasma catecholamines. Hypertensive animal models respond to diltiazem with reductions in blood pressure and increased urinary output and natriuresis without a change in the urinary sodium/potassium ratio. In man, transient natriuresis and kaliuresis have been reported, but only in high intravenous doses of 0.5 mg/kg of body weight.

Diltiazem-associated prolongation of the AH interval is not more pronounced in patients with first-degree heart block. In patients with sick sinus syndrome, diltiazem significantly prolongs sinus cycle length (up to 50% in some cases). Intravenous diltiazem in doses of 20 mg prolongs AH conduction time and AV node functional and effective refractory periods approximately 20%.

In two short-term, double-blind, placebo-controlled studies, 303 hypertensive patients were treated with once daily diltiazem hydrochloride extended-release capsules in doses of up to 540 mg. There were no instances of greater than first-degree atrioventricular block, and the maximum increase in the PR interval was 0.08 seconds. No patients were prematurely discontinued from the medication due to symptoms related to prolongation of the PR interval.

Pharmacodynamics

In one short-term, double-blind, placebo-controlled study, diltiazem hydrochloride extended-release capsules 120, 240, 360, and 480 mg/day demonstrated a dose-related antihypertensive response among patients with mild to moderate hypertension. Statistically significant decreases in trough mean supine diastolic blood pressure were seen through 4 weeks of treatment: 120 mg/day (-5.1 mmHg); 240 mg/day (-6.9 mmHg); 360 mg/day (-6.9 mmHg); and, 480 mg/day (-10.6 mmHg). Statistically significant decreases in trough mean supine systolic blood pressure were also seen through 4 weeks of treatment: 120 mg/day (-2.6 mmHg); 240 mg/day (-6.5 mmHg); 360 mg/day (-4.8 mmHg); and 480 mg/day (-10.6 mmHg). The proportion of evaluable patients exhibiting a therapeutic response (supine diastolic blood pressure <90 mmHg or decrease >10 mmHg) was greater as the dose increased: 31%, 42%, 48%, and 69% with the 120, 240, 360, and 480 mg/day diltiazem groups, respectively. Similar findings were observed for standing systolic and diastolic blood pressures. The trough (24 hours after a dose) antihypertensive effect of diltiazem hydrochloride extended-release capsules retained more than one-half of the response seen at peak (3 to 6 hours after administration).

Significant reductions of mean supine blood pressure (at trough) in patients with mild to moderate hypertension were also seen in a short-term, double-blind, dose-escalation, placebo-controlled study after 2 weeks of once daily diltiazem hydrochloride extended-release capsules 180 mg/day (diastolic: -6.1 mmHg; systolic: -4.7 mmHg) and again, 2 weeks after escalation to 360 mg/day (diastolic: -9.3 mmHg; systolic: -7.2 mmHg). However, a further increase in dose to 540 mg/day for 2 weeks provided only a minimal further increase in the antihypertensive effect (diastolic: -10.2 mmHg; systolic: -6.7 mmHg).

Diltiazem hydrochloride extended-release capsules, given at 120 mg, 240 mg, and 480 mg/day, in a randomized, multicenter, double-blind, placebo-controlled, parallel group, dose-ranging study, in 189 patients with chronic angina, demonstrated a dose-related increase in exercise time by Exercise Tolerance Test (ETT) and a reduction in rates of anginal attacks (based on individual patient diaries). The improvement in total exercise time (using the Bruce protocol), measured at trough exercise periods, for placebo, 120 mg, 240 mg, and 480 mg, was 20, 37, 49, and 56 seconds, respectively.

Pharmacokinetics and Metabolism

Diltiazem is well absorbed from the gastrointestinal tract, and is subject to an extensive first-pass effect. When given as an immediate release oral formulation, the absolute bioavailability (compared to intravenous administration) of diltiazem is approximately 40%. Diltiazem undergoes extensive hepatic metabolism in which 2% to 4% of the unchanged drug appears in the urine. Total radioactivity measurement following short IV administration in healthy volunteers suggests the presence of other unidentified metabolites which attain higher concentrations than those of diltiazem and are more slowly eliminated; half-life of total radioactivity is about 20 hours compared to 2 to 5 hours for diltiazem. In vitrobinding studies show diltiazem HCl is 70% to 80% bound to plasma proteins. Competitive in vitroligand binding studies have also shown diltiazem HCl binding is not altered by therapeutic concentrations of digoxin, HCTZ, phenylbutazone, propranolol, salicylic acid, or warfarin. The plasma elimination half-life of diltiazem is approximately 3.0 to 4.5 hours. Desacetyldiltiazem, the major metabolite of diltiazem, which is also present in the plasma at concentrations of 10% to 20% of the parent drug, is approximately 25% to 50% as potent a coronary vasodilator as diltiazem. Therapeutic blood levels of diltiazem hydrochloride appear to be in the range of 40 to 200 ng/mL. There is a departure from linearity when dose strengths are increased; the half-life is slightly increased with dose.

A study that compared patients with normal hepatic function to patients with cirrhosis found an increase in half-life and a 69% increase in bioavailability in the hepatically impaired patients. Patients with severely impaired renal function showed no difference in the pharmacokinetic profile of diltiazem compared to patients with normal renal function.

Diltiazem hydrochloride extended-release capsules contain a degradable controlled-release tablet formulation designed to release diltiazem over a 24-hour period. Controlled absorption of diltiazem begins within 1 hour, with maximum plasma concentrations being achieved 4 to 6 hours after administration. The apparent steady-state half-life of diltiazem following once daily administration of diltiazem hydrochloride extended-release capsules ranges from 5 to 10 hours. This prolongation of half-life is attributed to continued absorption of diltiazem rather than to alterations in its elimination.

The absolute bioavailability of diltiazem from a single dose of diltiazem hydrochloride extended-release capsules (compared to intravenous administration) is 41% (± 14). The value was shown to be similar to the 40% systemic availability reported following administration of an immediate release diltiazem HCl formulation.

As the dose of diltiazem hydrochloride extended-release capsules is increased from a daily dose of 120 mg to 240 mg, there is an increase in the AUC of 2.3 fold. When the dose is increased from 240 mg to 360 mg, AUC increases 1.6 fold and when increased from 240 mg to 480 mg, AUC increases 2.4 fold.

In vivorelease of diltiazem occurs throughout the gastrointestinal tract, with controlled release still occurring for up to 24 hours after administration, as determined by radio-labeled methods. As the once daily dose of diltiazem hydrochloride extended-release capsules was increased, departures from linearity were noted. There were disproportionate increases in area under the curve for doses from 120 mg to 480 mg.

The presence of food did not affect the ability of diltiazem hydrochloride extended-release capsules to maintain a controlled release of the drug and did not impact its sustained release properties over 24-hours after administration. However, simultaneous administration of diltiazem hydrochloride extended-release capsules with a high-fat breakfast resulted in increases in AUC of 13% and 19%, and in Cmaxby 37% and 51%, respectively.

INDICATIONS AND USAGE

Diltiazem Hydrochloride Extended-Release Capsules are indicated for the treatment of hypertension. Diltiazem hydrochloride may be used alone or in combination with other antihypertensive medications, such as diuretics.

Diltiazem Hydrochloride Extended-Release Capsules are indicated for the management of chronic stable angina.

CONTRAINDICATIONS

Diltiazem hydrochloride is contraindicated in: (1) patients with sick sinus syndrome except in the presence of a functioning ventricular pacemaker; (2) patients with second or third degree AV block except in the presence of a functioning ventricular pacemaker; (3) patients with hypotension (less than 90 mmHg systolic); (4) patients who have demonstrated hypersensitivity to the drug; and (5) patients with acute myocardial infarction and pulmonary congestion as documented by X-ray on admission.

WARNINGS

Cardiac Conduction

Diltiazem hydrochloride prolongs AV node refractory periods without significantly prolonging sinus node recovery time, except in patients with sick sinus syndrome. This effect may rarely result in abnormally slow heart rates (particularly in patients with sick sinus syndrome) or second, or third degree AV block (22 of 10,119 patients, or 0.2%); 41% of these 22 patients were receiving concomitant β-adrenoceptor antagonists versus 17% of the total group. Concomitant use of diltiazem with beta-blockers or digitalis may result in additive effects on cardiac conduction. A patient with Prinzmetal’s angina developed periods of asystole (2 to 5 seconds) after a single 60 mg dose of diltiazem.

Congestive Heart Failure

Although diltiazem has a negative inotropic effect in isolated animal tissue preparations, hemodynamic studies in humans with normal ventricular function have not shown a reduction in cardiac index nor consistent negative effects on contractility (dp/dt). An acute study of oral diltiazem in patients with impaired ventricular function (ejection fraction of 24% ± 6%) showed improvement in indices of ventricular function without significant decrease in contractile function (dp/dt). Worsening of congestive heart failure has been reported in patients with preexisting impairment of ventricular function. Experience with the use of diltiazem hydrochloride in combination with beta-blockers in patients with impaired ventricular function is limited. Caution should be exercised when using this combination.

Hypotension

Decreases in blood pressure associated with diltiazem hydrochloride therapy may occasionally result in symptomatic hypotension.

Acute Hepatic Injury

Mild elevations of serum transaminases with and without concomitant elevation in alkaline phosphatase and bilirubin have been observed in clinical studies. Such elevations were usually transient and frequently resolved even with continued diltiazem treatment. In rare instances, significant elevations in alkaline phoshatase, LDH, SGOT, SGPT, and other phenomena consistent with acute hepatic injury have been noted. These reactions tended to occur early after therapy initiation (1 to 6 weeks) and have been reversible upon discontinuation of drug therapy. The relationship to diltiazem is uncertain in some cases, but probable in some others. (See PRECAUTIONS.)

PRECAUTIONS

General

Diltiazem hydrochloride is extensively metabolized by the liver and is excreted by the kidneys and in bile. As with any drug given over prolonged periods, laboratory parameters should be monitored at regular intervals. The drug should be used with caution in patients with impaired renal or hepatic function. In subacute and chronic dog and rat studies designed to produce toxicity, high doses of diltiazem were associated with hepatic damage. In special subacute hepatic studies, oral doses of 125 mg/kg and higher in rats were associated with histological changes in the liver which were reversible when the drug was discontinued. In dogs, doses of 20 mg/kg were also associated with hepatic changes; however, these changes were reversible with continued dosing.

Dermatological events (see ADVERSE REACTIONS) may be transient and may disappear despite continued use of diltiazem hydrochloride. However, skin eruptions progressing to erythema multiforme and/or exfoliative dermatitis have also been infrequently reported. Should a dermatologic reaction persist, the drug should be discontinued.

Although diltiazem hydrochloride extended-release capsules utilize a slowly disintegrating matrix, caution should still be used in patients with preexisting severe gastrointestinal narrowing (pathologic or iatrogenic). There have been no reports of obstructive symptoms in patients with known strictures in association with the ingestion of diltiazem hydrochloride extended-release capsules.

Information for Patients

Diltiazem hydrochloride extended-release capsules should be taken on an empty stomach. Patients should be cautioned that the diltiazem hydrochloride extended-release capsules should not be opened, chewed or crushed, and should be swallowed whole.

Drug Interactions

Due to the potential for additive effects, caution and careful titration are warranted in patients receiving diltiazem hydrochloride concomitantly with any agents known to affect cardiac contractility and/or conduction. (See WARNINGS.) Pharmacologic studies indicate that there may be additive effects in prolonging AV conduction when using beta-blockers or digitalis concomitantly with diltiazem hydrochloride. (See WARNINGS.) As with all drugs, care should be exercised when treating patients with multiple medications. Diltiazem hydrochloride undergoes biotransformation by cytochrome P-450 mixed function oxidase. Co-administration of diltiazem hydrochloride with other agents which follow the same route of biotransformation may result in the competitive inhibition of metabolism. Especially in patients with renal and/or hepatic impairment, dosages of similarly metabolized drugs, particularly those of low therapeutic ratio such as cyclosporine, may require adjustment when starting or stopping concomitantly administered diltiazem hydrochloride to maintain optimum therapeutic blood levels. Concomitant administration of diltiazem with carbamazepine has been reported to result in elevated plasma levels of carbamazepine, resulting in toxicity in some cases.

Beta-Blockers

Controlled and uncontrolled domestic studies suggest that concomitant use of diltiazem hydrochloride and beta-blockers is usually well-tolerated, but available data are not sufficient to predict the effects of concomitant treatment in patients with left ventricular dysfunction or cardiac conduction abnormalities. Administration of diltiazem hydrochloride concomitantly with propranolol in five normal volunteers resulted in increased propranolol levels in all subjects and the bioavailability of propranolol was increased approximately 50%. If combination therapy is initiated or withdrawn in conjunction with propranolol, an adjustment in the propranolol dose may be warranted. (See WARNINGS.)

Cimetidine

A study in six healthy volunteers has shown a significant increase in peak diltiazem plasma levels (58%) and area-under-the-curve (53%) after a 1 week course of cimetidine at 1,200 mg per day and diltiazem 60 mg per day. Ranitidine produced smaller, nonsignificant increases. The effect may be mediated by cimetidine’s known inhibition of hepatic cytochrome P-450, the enzyme system responsible for the first-pass metabolism of diltiazem. Patients currently receiving diltiazem therapy should be carefully monitored for a change in pharmacological effect when initiating and discontinuing therapy with cimetidine. An adjustment in the diltiazem dose may be warranted.

Clonidine

Sinus bradycardia resulting in hospitalization and pacemaker insertion has been reported in association with the use of clonidine concurrently with diltiazem. Monitor heart rate in patients receiving concomitant diltiazem and clonidine.

Digitalis

Administration of diltiazem hydrochloride with digoxin in 24 healthy male subjects increased plasma digoxin concentrations approximately 20%. Another investigator found no increase in digoxin levels in 12 patients with coronary artery disease. Since there have been conflicting results regarding the effects of digoxin levels, it is recommended that digoxin levels be monitored when initiating, adjusting, and discontinuing diltiazem hydrochloride therapy to avoid possible over- or under-digitalization. (See WARNINGS.)

Anesthetics

The depression of cardiac contractility, conductivity, and automaticity as well as the vascular dilation associated with anesthetics may be potentiated by calcium channel blockers. When used concomitantly, anesthetics and calcium channel blockers should be titrated carefully.

Statins

Diltiazem is an inhibitor of CYP3A4 and has been shown to increase significantly the AUC of some statins. The risk of myopathy and rhabdomyolysis with statins metabolized by CYP3A4 may be increased with concomitant use of diltiazem. When possible, use a non-CYP3A4-metabolized statin with diltiazem; otherwise, dose adjustments for both diltiazem and the statin should be considered along with close monitoring for signs and symptoms of any statin related adverse events.

In a healthy volunteer cross-over study (N=10), co-administration of a single 20 mg dose of simvastatin at the end of a 14 day regimen with 120 mg twice daily diltiazem SR resulted in a 5-fold higher mean simvastatin AUC compared with simvastatin alone. High average steady-state exposures of diltiazem would result in a greater increase in simvastatin exposure. A daily dose of 480 mg of diltiazem would be expected to result in an 8-fold higher mean simvastatin AUC compared with simvastatin alone. If coadministration of simvastatin with diltiazem is required, limit the daily doses of simvastatin to 10 mg and diltiazem to 240 mg.

In a ten-subject randomized, open label, 4-way cross-over study, co-administration of diltiazem (120 mg twice daily diltiazem SR for 2 weeks) with a single 20 mg dose of lovastatin resulted in 3- to 4- fold higher mean lovastatin AUC and Cmaxvalues compared with lovastatin alone. In the same study, there was no significant change in 20 mg single dose pravastatin AUC and Cmaxduring diltiazem coadministration.

Carcinogenesis, Mutagenesis, Impairment of Fertility

A 24-month study in rats and an 18-month study in mice showed no evidence of carcinogenicity. There was also no mutagenic response in vitroor in vivoin mammalian cell assays or in vitroin bacteria. No evidence of impaired fertility was observed in male or female rats at oral doses of up to 100 mg/kg/day.

Pregnancy

Reproduction studies have been conducted in mice, rats, and rabbits. Administration of doses ranging from 4 to 6 times (depending on species) the upper limit of the optimum dosage range in clinical trials (480 mg once daily or 8 mg/kg once daily for a 60 kg patient) has resulted in embryo and fetal lethality. These studies have revealed, in one species or another, a propensity to cause abnormalities of the skeleton, heart, retina, and tongue. Also observed were reductions in early individual pup weights and pup survival, prolonged delivery, and increased incidence of stillbirths.

There are no well-controlled studies in pregnant women; therefore, use diltiazem hydrochloride in pregnant women only if the potential benefit justifies the potential risk to the fetus.

Nursing Mothers

Diltiazem is excreted in human milk. One report suggests that concentrations in breast milk may approximate serum levels. If use of diltiazem hydrochloride is deemed essential, an alternate method of infant feeding should be instituted.

Pediatric Use

Safety and effectiveness in pediatric patients have not been established.

ADVERSE REACTIONS

Serious adverse reactions to diltiazem hydrochloride have been rare in studies with other formulations, as well as with diltiazem hydrochloride extended-release capsules. It should be recognized, however, that patients with impaired ventricular function and cardiac conduction abnormalities have usually been excluded from these studies.

Hypertension

The most common adverse events (frequency ≥1%) in placebo-controlled, clinical hypertension studies with diltiazem hydrochloride extended-release capsules using daily doses up to 540 mg, are listed in the table below with placebo-treated patients included for comparison.

MOST COMMON ADVERSE EVENTS IN DOUBLE-BLIND, PLACEBO-CONTROLLED HYPERTENSION TRIALS
Adverse Events | Diltiazem Hydrochloride Extended-Release Capsules [Adverse events occurring in 1% or more of patients receiving diltiazem hydrochloride extended-release capsules.] | Placebo
(COSTART Term) | n=303 # pts (%) | n=87 # pts (%)
rhinitis | 29 (9.6) | 7 (8.0)
headache | 27 (8.9) | 12 (13.8)
pharyngitis | 17 (5.6) | 4 (4.6)
constipation | 11 (3.6) | 2 (2.3)
cough increase | 9 (3.0) | 2 (2.3)
flu syndrome | 7 (2.3) | 1 (1.1)
edema, peripheral | 7 (2.3) | 0 (0.0)
myalgia | 7 (2.3) | 0 (0.0)
diarrhea | 6 (2.0) | 0 (0.0)
vomiting | 6 (2.0) | 0 (0.0)
sinusitis | 6 (2.0) | 1 (1.1)
asthenia | 5 (1.7) | 0 (0.0)
pain, back | 5 (1.7) | 2 (2.3)
nausea | 5 (1.7) | 1 (1.1)
dyspepsia | 4 (1.3) | 0 (0.0)
vasodilatation | 4 (1.3) | 0 (0.0)
injury, accident | 4 (1.3) | 0 (0.0)
pain, abdominal | 3 (1.0) | 0 (0.0)
arthrosis | 3 (1.0) | 0 (0.0)
insomnia | 3 (1.0) | 0 (0.0)
dyspnea | 3 (1.0) | 0 (0.0)
rash | 3 (1.0) | 1 (1.1)
tinnitus | 3 (1.0) | 0 (0.0)

Angina

The most common adverse events (frequency ≥1%) in a placebo-controlled, short-term (2 week) clinical angina study with diltiazem hydrochloride extended-release capsules are listed in the table below with placebo-treated patients included for comparison. In this trial, following a placebo phase, patients were randomly assigned to once daily doses of either 120, 240, or 480 mg of diltiazem hydrochloride extended-release capsules.

MOST COMMON ADVERSE EVENTS IN A DOUBLE-BLIND, PLACEBO-CONTROLLED SHORT-TERM, ANGINA TRIALS
Adverse Events | Diltiazem Hydrochloride Extended-Release Capsules [Adverse events occurring in 1% or more of patients receiving diltiazem hydrochloride extended-release capsules.] | Placebo
(COSTART Term) | n=139 # pts (%) | n=50 # pts (%)
asthenia | 5 (3.6) | 2 (4.0)
headache | 4 (2.9) | 3 (6.0)
pain, back | 4 (2.9) | 1 (2.0)
rhinitis | 4 (2.9) | 1 (2.0)
constipation | 3 (2.2) | 1 (2.0)
nausea | 3 (2.2) | 0 (0.0)
edema, peripheral | 3 (2.2) | 1 (2.0)
dizziness | 3 (2.2) | 0 (0.0)
cough, increased | 3 (2.2) | 0 (0.0)
bradycardia | 2 (1.4) | 0 (0.0)
fibrillation, atrial | 2 (1.4) | 0 (0.0)
arthralgia | 2 (1.4) | 0 (0.0)
dream, abnormal | 2 (1.4) | 0 (0.0)
dyspnea | 2 (1.4) | 0 (0.0)
pharyngitis | 2 (1.4) | 1 (2.0)

Infrequent Adverse Events

The following additional events (COSTART Terms), listed by body system, were reported infrequently (less than 1%) in all subjects, hypertensive (n=425) or angina (n=318) patients who received diltiazem hydrochloride extended-release capsules, or with other formulations of diltiazem.

Hypertension

Cardiovascular:First-degree AV block, arrhythmia, postural hypotension, tachycardia, pallor, palpitations, phlebitis, ECG abnormality, ST elevation.

Nervous System:Vertigo, hypertonia, paresthesia, dizziness, somnolence.

Digestive System:Dry mouth, anorexia, tooth disorder, eructation.

Skin and Appendages:Sweating, urticaria, skin hypertrophy (nevus).

Respiratory System:Epistaxis, bronchitis, respiratory disorder.

Urogenital System:Cystitis, kidney calculus, impotence, dysmenorrhea, vaginitis, prostate disease.

Metabolic and Nutritional Disorders:Gout, edema.

Musculoskeletal System:Arthralgia, bursitis, bone pain.

Hemic and Lymphatic System:Lymphadenopathy.

Body as a Whole:Pain, unevaluable reaction, neck pain, neck rigidity, fever, chest pain, malaise.

Special Senses:Amblyopia (blurred vision), ear pain.

Angina

Cardiovascular:Palpitations, AV block, sinus bradycardia, bigeminal extrasystole, angina pectoris, hypertension, hypotension, myocardial infarct, myocardial ischemia, syncope, vasodilatation, ventricular extrasystole.

Nervous System:Abnormal thinking, neuropathy, paresthesia.

Digestive System:Diarrhea, dyspepsia, vomiting, colitis, flatulence, GI hemorrhage, stomach ulcers.

Skin and Appendages:Contact dermatitis, pruritus, sweating.

Respiratory System:Respiratory distress.

Urogenital System:Kidney failure, pyelonephritis, urinary tract infection.

Metabolic and Nutritional Disorders:Weight increase.

Musculoskeletal System:Myalgia.

Body as a Whole:Chest pain, accidental injury, infection.

Special Senses:Eye hemorrhage, ophthalmitis, otitis media, taste perversion, tinnitus.

There have been post-marketing reports of Stevens-Johnson syndrome and toxic epidermal necrolysis associated with the use of diltiazem hydrochloride.

OVERDOSAGE OR EXAGGERATED RESPONSE

Several literature reports have identified cases of diltiazem hydrochloride overdose, some with multiple drug ingestion, with both fatal and non-fatal outcomes. The reported events affected multiple body systems including the cardiovascular system (bradycardia, complete heart block, asystole, cardiac failure, arrhythmia, atrial fibrillation, palpitations, hypotension, ischemia, ECG changes), respiratory system (respiratory failure, hypoxia, dyspnea, pulmonary edema), central nervous system (loss of consciousness, convulsions, dizziness, confusion, agitation), gastrointestinal system (nausea, vomiting), skin and appendages (increased sweating), and other systems (hypotonia, iliac artery thrombosis, metabolic acidosis, increased blood glucose). The administration of ipecac to induce vomiting and activated charcoal to reduce drug absorption have been advocated as initial means of intervention. In addition to gastric lavage, the following measures should also be considered:

Bradycardia:administer atropine (0.6 mg to 1 mg). If there is no response to vagal blockade, administer isoproterenol cautiously.

High-Degree AV Block:Treat as for bradycardia above. Fixed high-degree AV block should be treated with cardiac pacing.

Cardiac Failure:Administer inotropic agents (dopamine or dobutamine) and diuretics.

Hypotension:Vasopressors (e.g., dopamine or levarterenol bitartrate).

Actual treatment and dosage should depend on the severity of the clinical situation as well as the judgment and experience of the treating physician.

Due to extensive metabolism, plasma concentrations after a standard dose of diltiazem can vary over tenfold, which significantly limits their value in evaluating cases of overdosage.

Charcoal hemoperfusion has been used successfully as an adjunct therapy to hasten drug elimination. Overdoses with as much as 10.8 grams of oral diltiazem have been successfully treated using appropriate supportive care.

DOSAGE AND ADMINISTRATION

Hypertensive or anginal patients who are treated with other formulations of diltiazem can safely be switched to diltiazem hydrochloride extended-release capsules at the nearest equivalent total daily dose. Subsequent titration to higher or lower doses may, however, be necessary and should be initiated as clinically indicated.

Studies have shown a slight increase in the rate of absorption of diltiazem hydrochloride extended-release capsules when ingested with a high-fat breakfast; therefore, administration in the morning on an empty stomach is recommended.

Patients should be cautioned that the diltiazem hydrochloride extended-release capsules should not be opened, chewed or crushed, and should be swallowed whole.

Dosage

Hypertension

Dosages must be adjusted to each patient’s needs, starting with 180 mg or 240 mg once daily. Based on the antihypertensive effect, the dose may be adjusted as needed. Individual patients, particularly ≥60 years of age, may respond to a lower dose of 120 mg. The usual dosage range studied in clinical trials was 180 mg to 480 mg once daily.

Current clinical experience with the 540 mg dose is limited; the dose may be increased to 540 mg with little or no increased risk of adverse reactions. Doses should not exceed 540 mg once daily.

While a dose of diltiazem hydrochloride extended-release capsules given once daily may produce an antihypertensive effect similar to the same total daily dose given in divided doses, individual dose adjustment may be needed.

Dosage

Angina

Dosages for the treatment of angina should be adjusted to each patient’s needs, starting with a dose of 120 mg once daily, which may be titrated to doses of up to 480 mg once daily. When necessary, titration may be carried out over a 7 to 14 day period.

Concomitant Use with Other Cardiovascular Agents.

Sublingual Nitroglycerinmay be taken as required to abort acute anginal attacks during diltiazem hydrochloride therapy.

Prophylactic Nitrate Therapy– Diltiazem hydrochloride may be safely co-administered with short- and long-acting nitrates.

Beta-blockers.(See WARNINGSand PRECAUTIONS.)

Antihypertensives– Diltiazem hydrochloride has an additive antihypertensive effect when used with other antihypertensive agents. Therefore, the dosage of diltiazem hydrochloride or the concomitant antihypertensives may need to be adjusted when adding one to the other.

HOW SUPPLIED

Diltiazem Hydrochloride Extended-Release Capsules, USP are supplied as follows:

- 120 mg capsules, opaque yellow cap and white body, imprinted with and ‘148’ on the cap in black ink.

NDC 70436-191-01, bottles of 100 capsules with child-resistant closure.
NDC 70436-191-02, bottles of 500 capsules.

- 180 mg capsules, opaque light orange cap and white body, imprinted with and ‘149’ on the cap in black ink.

NDC 70436-192-01, bottles of 100 capsules with child-resistant closure.
NDC 70436-192-02, bottles of 500 capsules.

- 240 mg capsules, opaque chocolate brown cap and white body, imprinted with on the cap and ‘150’ on the body in black ink.

NDC 70436-193-01, bottles of 100 capsules with child-resistant closure.
NDC 70436-193-02, bottles of 500 capsules.

Store at 20° to 25°C (68° to 77°F); excursions permitted to 15° to 30°C (59° to 86°F) [See USP Controlled Room Temperature].

Dispense in a tight, light-resistant container as defined in the USP with a child-resistant closure.

Keep this and all drugs out of the reach of children.

Distributed by:
Slate Run Pharmaceuticals, LLC, Columbus, Ohio 43215 USA

Rev. 07/2025
10000545/01

PACKAGE LABEL

PRINCIPAL DISPLAY PANEL

Diltiazem hydrochloride 120 mg Capsules- Label

NDC 70436-191-01

Diltiazem Hydrochloride Extended-Release Capsules, USP

120 mg

Rx

100 count

NDC 70436-191-02

Diltiazem Hydrochloride Extended-Release Capsules, USP

120 mg

Rx

500 count

Diltiazem hydrochloride 180 mg Capsules- Label

NDC 70436-192-01

Diltiazem Hydrochloride Extended-Release Capsules, USP

180 mg

Rx

100 count

NDC 70436-192-02

Diltiazem Hydrochloride Extended-Release Capsules, USP

180 mg

Rx

500 count

Diltiazem hydrochloride 240 mg Capsules- Label

NDC 70436-193-01

Diltiazem Hydrochloride Extended-Release Capsules, USP

240 mg

Rx

100 count

NDC 70436-193-02

Diltiazem Hydrochloride Extended-Release Capsules, USP

240 mg

Rx

500 count